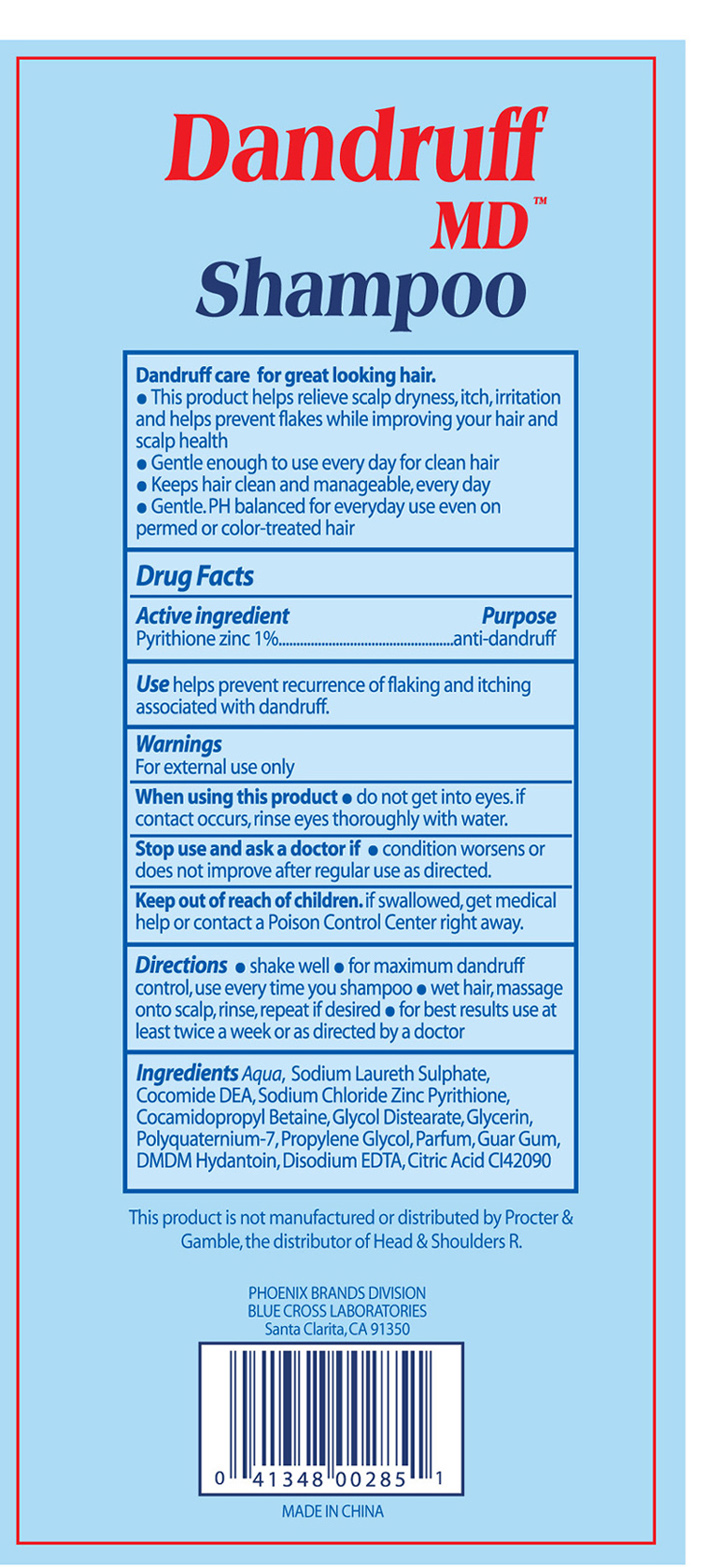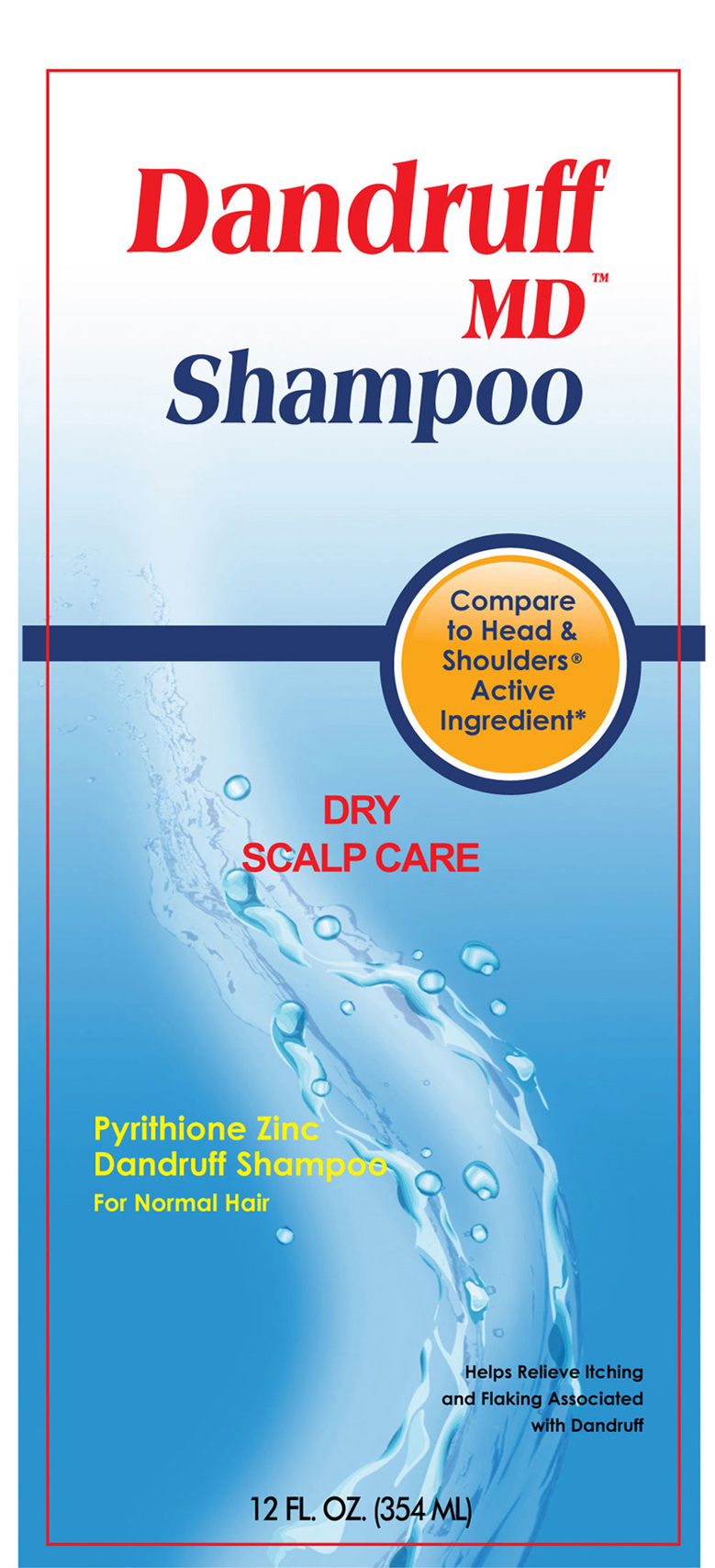 DRUG LABEL: Dry Scalp Care
NDC: 22431-580 | Form: SHAMPOO
Manufacturer: Blue Coss Laboratories, Inc. 
Category: otc | Type: HUMAN OTC DRUG LABEL
Date: 20121205

ACTIVE INGREDIENTS: PYRITHIONE ZINC 1 mL/100 mL
INACTIVE INGREDIENTS: SODIUM LAURETH SULFATE; COCO DIETHANOLAMIDE; COCAMIDOPROPYL BETAINE; GLYCOL DISTEARATE; GLYCERIN; PROPYLENE GLYCOL; DMDM HYDANTOIN; EDETATE DISODIUM; CITRIC ACID MONOHYDRATE

Dandruff MD Shampoo

Active Ingredient Purpose

Pyrithione Zinc 1% anti-dandruff

PURPOSE

Use: Helps prevent recurrence of flaking and itching associated with dandruff

Keep out of reach of children. If swallowed, get medical help or contact a poison control center right away.

Stop use and ask a doctor if

condition worsens or does not improve after regular use as directed.

Warnings: For external use only.

When using this product: Do not get into eyes. If contact occurs, rinse eyes thoroughly with water.

Directions:

Shake well.

For maximum dandruff control, use every time you shampoo.

Wet Hair, massage onto scalp, rinse, repeat if desired.

For best results use at least twice a week or as directed by a doctor.

INACTIVE INGREDIENT

Inactive Ingredients: Aqua, Sodium Laureth Sulphate, Cocomide DEA, Sodium Chloride Zinc Pyrithione, Cocamidopropyl Betaine, Glycol Distearate, Glycerin, Polyquaternum-7, Propylene Glycol, Parfum, Guar Gum, DMDM Hydantoin, Disodium EDTA, Citric Acid CI 42090

PACKAGE LABEL

Dandruff MD Shampoo 12 FL. OZ. (354 ML)